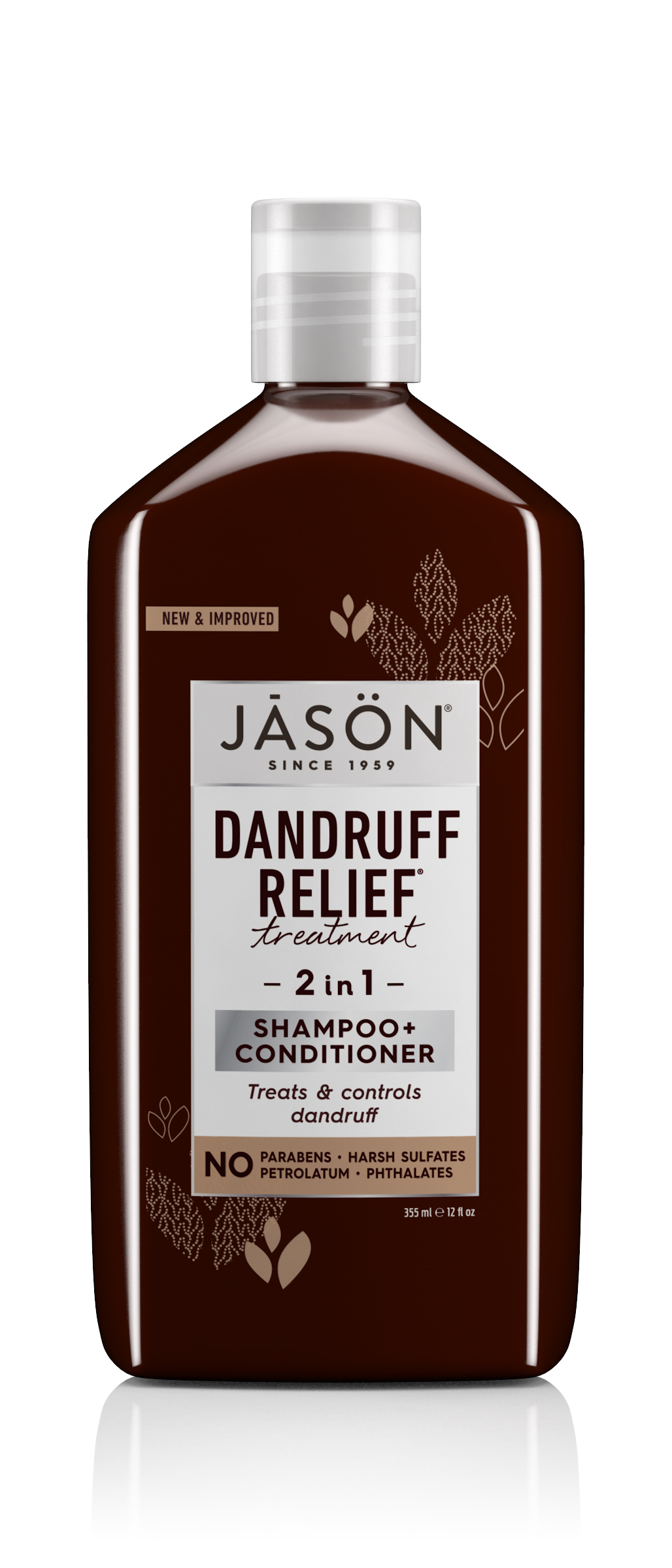 DRUG LABEL: J1002902 Jason Dandruff Relief 2in1 Treatment
NDC: 61995-2439 | Form: SHAMPOO
Manufacturer: The Hain Celestial Group Inc
Category: otc | Type: HUMAN OTC DRUG LABEL
Date: 20251001

ACTIVE INGREDIENTS: PYRITHIONE ZINC 1.1 g/100 g
INACTIVE INGREDIENTS: COCAMIDOPROPYL HYDROXYSULTAINE 4.7 g/100 g; SODIUM CHLORIDE 1.4 g/100 g; CETYL ALCOHOL 5 g/100 g; SODIUM COCOYL ISETHIONATE 5 g/100 g; GLYCERYL STEARATE SE 2 g/100 g; MEDIUM-CHAIN TRIGLYCERIDES 1.2 g/100 g; WATER 66.7 g/100 g; GLYCERIN 5 g/100 g; STEARYL ALCOHOL 3 g/100 g; DISODIUM COCOYL GLUTAMATE 1.5 g/100 g

J1002902 Jason Dandruff Relief 2in1 Treatment

Act Ingred - Jason Dandruff Relief Treatment 2-in-1 Shampoo & Conditioner

Active Ingredient:

Zinc Pyrithione 1.0%

KOORC - Jason Dandruff Relief Treatment 2-in-1 Shampoo & Conditioner

Warnings:

Keep out of reach of children. If swallowed, get medical help or contact a Poison Control Center right away.

Purpose - Jason Dandruff Relief Treatment 2-in-1 Shampoo & Conditioner

Purpose:

Controls dandruff

D&A - Jason Dandruff Relief Treatment 2-in-1 Shampoo & Conditioner

Directions:

For best results use at least three times each week. Wet hair and lather, massage onto scalp. Rinse and repeat if desired.

Warnings - Jason Dandruff Relief Treatment 2-in-1 Shampoo & Conditioner

Warnings.

For external use only. Avoid contact with eyes. Rinse eyes thoroughly with water in case contact occurs. Discontinue use and consult your physician if irritation develops. Keep out of reach of children. If swallowed, get medical help or contact a Poison Control Center right away.

Indication & Use - Jason Dandruff Relief Treatment 2-in-1 Shampoo & Conditioner

Uses:

- Controls recurrance of flaking, scaling, and itching associated with dandruff
- Helps prevent seborrheic dermatitis

Inactives - Jason Dandruff Relief Treatment 2-in-1 Shampoo & Conditioner

Inactive ingredients:

Water (Aqua), Sodium Cocoyl Isethionate, Cetyl Alcohol, Glycerin, Cocamidopropyl Hydroxysultaine, Sodium Laurylglucosides Hydroxypropylsulfonate, Sodium Cocoyl Glutamate, Sodium Chloride, Glyceryl Stearate SE, Coco-Glucoside, Glyceryl Oleate, Butyrospermum Parkii (Shea) Butter Unsaponifiables, Citrus Aurantium Dulcis (Orange) Peel Oil, Olea Europaea (Olive) Fruit Oil (1), Simmondsia Chinensis (Jojoba) Seed Oil (1), Soybean Glycerides, Chenopodium Quinoa Seed (1), Ascorbyl Palmitate, Babassu Oil Polyglyceryl-4 Esters, Benzyl Acetate, Caprylic/Capric Triglyceride, Capryloyl Glycerin/Sebacic Acid Copolymer, Cellulose Gum, Citric Acid, Diheptyl Succinate, Guar Hydroxypropyltrimonium Chloride, Phenethyl Alcohol, Sodium Hydroxide, Sodium PCA, Terpineol, Triethyl Citrate, Xanthan Gum, Zinc Carbonate, Alcohol (1), Ethylhexylglycerin, Phenoxyethanol, Potassium Sorbate, Limonene, Linalool.